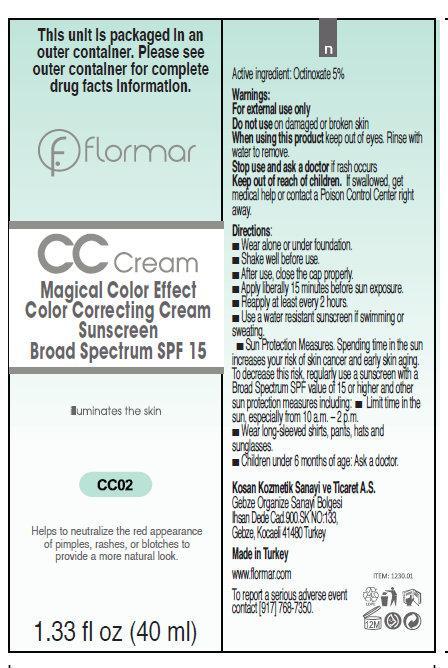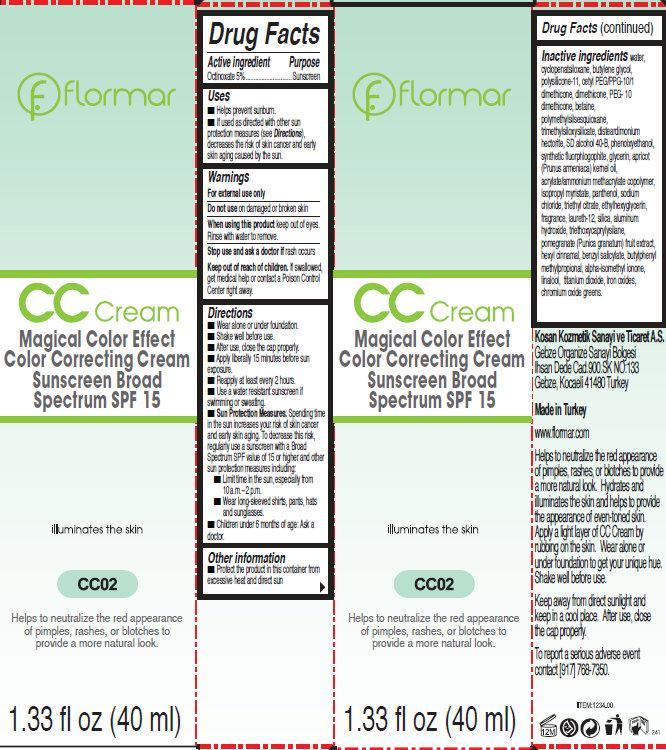 DRUG LABEL: flormar CC Magical Color Effect Color Correcting Cream Sunscreen Broad Spectrum SPF 15 CC02
NDC: 61722-140 | Form: CREAM
Manufacturer: Kosan Kozmetik Sanayi ve Ticaret A.S.
Category: otc | Type: HUMAN OTC DRUG LABEL
Date: 20191018

ACTIVE INGREDIENTS: OCTINOXATE 50 mg/1 mL
INACTIVE INGREDIENTS: WATER; CYCLOMETHICONE 5; BUTYLENE GLYCOL; DIMETHICONE; BETAINE; DISTEARDIMONIUM HECTORITE; PHENOXYETHANOL; GLYCERIN; ISOPROPYL MYRISTATE; PANTHENOL; SODIUM CHLORIDE; TRIETHYL CITRATE; ETHYLHEXYLGLYCERIN; LAURETH-12; SILICON DIOXIDE; ALUMINUM HYDROXIDE; TRIETHOXYCAPRYLYLSILANE; .ALPHA.-HEXYLCINNAMALDEHYDE; BENZYL SALICYLATE; BUTYLPHENYL METHYLPROPIONAL; ISOMETHYL-.ALPHA.-IONONE; LINALOOL, (+/-)-; TITANIUM DIOXIDE; FERRIC OXIDE RED; CHROMIC OXIDE

flormar CC Cream Magical Color Effect Color Correcting Cream Sunscreen Broad Spectrum SPF 15 CC02

Active Ingredient

Octinoxate 5%

Purpose

Sunscreen

Uses

- Helps prevent sunburn.
- If used as directed with other sun protection measures (see Directions), decreases the risk of skin cancer and early skin aging caused by the sun.

Warnings

For external use only

Do not use

on damaged or broken skin

When using this product

keep out of eyes. Rinse with water to remove.

Stop use and ask a doctor if

rash occurs

Keep out of reach of children.

If swallowed, get medical help or contact a Poison Control Center right away.

Directions

- Wear alone or under foundation.
- Shake well before use.
- Apply drop by drop with fingertips.
- Apply liberally 15 minutes before sun exposure.
- Reapply at least every 2 hours.
- Use a water resistant sunscreen if swimming or sweating.
- Sun Protection Measures. Spending time in the sun increases your risk of skin cancer and early skin aging. To decrease this risk, regularly use a sunscreen with a Broad Spectrum SPF value of 15 or higher and other sun protection measures including:
-
  - Limit time in the sun, especially from 10 a.m. – 2 p.m.
  - Wear long-sleeved shirts, pants, hats and sunglasses.
- Children under 6 months of age: Ask a doctor.

Other information

- Protect the product in this container from excessive heat and direct sun

Inactive ingredients

water, cyclopentasiloxane, butylene glycol, polysilicone-11, cetyl peg/ppg-10/1 dimethicone, dimethicone, peg-10 dimethicone, betaine, polymethylsilsesquioxane, trimethylsiloxysilicate, disteardimonium hectorite, sd alcohol 40-b, phenoxyethanol, synthetic fluorphlogophite, glycerin, apricot (prunus armeniaca) kernel oil, acrylate/ammonium methacrylate copolymer, isopropyl myristate, panthenol, sodium chloride, triethyl citrate, ethylhexylglycerin, tragrance, laureth-12, silica, aluminum hydroxide, triethoxycaprylysilane, pomegranate (punica granatum) fruit extract, hexyl cinnamal, benzyl salicylate, butylphenyl methylpropional, alpha-isomethyl ionone, linalool, titanium dioxide, iron oxides, chromium oxide greens